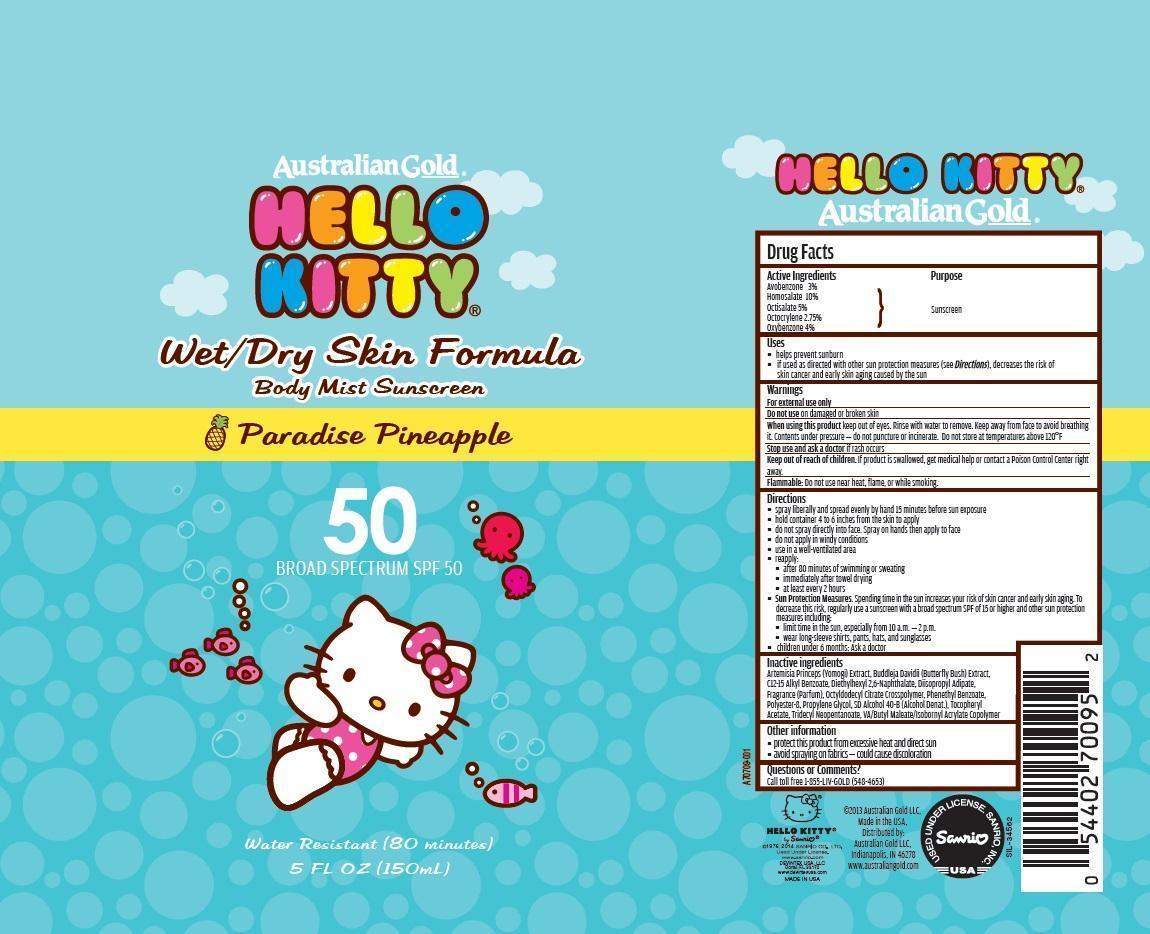 DRUG LABEL: Australian Gold
NDC: 13630-0087 | Form: AEROSOL, SPRAY
Manufacturer: Prime Packaging, Inc.
Category: otc | Type: HUMAN OTC DRUG LABEL
Date: 20200117

ACTIVE INGREDIENTS: AVOBENZONE 26.7 mg/1 mL; HOMOSALATE 89 mg/1 mL; OCTISALATE 44.5 mg/1 mL; OCTOCRYLENE 24.5 mg/1 mL; OXYBENZONE 35.6 mg/1 mL
INACTIVE INGREDIENTS: ALKYL (C12-15) BENZOATE; DIETHYLHEXYL 2,6-NAPHTHALATE; DIISOPROPYL ADIPATE; TRIOCTYLDODECYL CITRATE; PHENETHYL BENZOATE; POLYESTER-8 (1400 MW, CYANODIPHENYLPROPENOYL CAPPED); ALCOHOL; WATER; .ALPHA.-TOCOPHEROL ACETATE; TRIDECYL NEOPENTANOATE; DIBUTYL MALEATE; PROPYLENE GLYCOL; ARTEMISIA PRINCEPS LEAF; BUDDLEJA DAVIDII LEAF; ISOBORNYL ACRYLATE

Active ingredients

Avobenzone 3 %, Homosalate 10 %, Octisalate 5 %, Octocrylene 2.75 % and Oxybenzone 4 %

Purpose

Sunscreen

Uses

- helps prevent sunburn
- if used as directed with other sun protection measures (see Directions), decreases the risk of skin cancer and early skin aging caused by the sun

Warnings

OTHER SAFETY INFORMATION

For external use only

Do not use on broken or damaged skin

When using this product keep out of eyes. Rinse with water to remove. Keep away from face to avoid breathing it. Contents under pressure - do not puncture or incinirate. Do not store at temperatures above 120^0F

Stop use and ask a doctor if rash occurs.

Keep out of reach of children. If product is swallowed, get medical help or contact a Poison Control Center right away.

OTHER SAFETY INFORMATION

Flammable: Do not use near heat, flame or while smoking

Directions

- spray liberally and spread evenly by hand 15 minutes before sun exposure
- hold container 4 to 6 inches from the skin to apply
- do not spray directly into face. Spray on hands then apply to face
- do not apply in windy conditions
- use in well-ventilated areas
- reapply:
  - after 80 minutes of swimming or sweating
  - immediately after towel drying
  - at least every 2 hours
- Sun Protection Measures. Spending time in the sun increases your risk of skin cancer and early skin aging. To decrease this risk, regularly use a sunscreen with broad spectrum SPF of 15 or higher and other sun protection measures including:
  - limit time in the sun, especially from 10 a.m. – 2 p.m.
  - wear long-sleeve shirts, pants, hats, and sunglasses
- Children under 6 months: Ask a doctor

Inactive Ingredients

Artemisia Princeps (Yomogi) Extract, Buddleja Davidii (Butterfly Bush) Extract, C12-15 Alkyl Benzoate, Diethylhexyl 2,6-Naphthalate, Diisopropyl Adipate, Fragrance (Parfum), Octyldodecyl Citrate Crosspolymer, Phenethyl Benzoate, Polyester-8, Propylene Glycol, SD Alcohol 40-B (Alcohol Denat.), Tocopheryl Acetate, Tridecyl Neopentanoate, VA/Butyl Maleate/Isobornyl Acrylate Copolymer

Other information

- protect this product from excesive heat and direct sun
- avoid spraying on fabrics - could cause discoloration

Questions or Comments?

Call toll free 1-855-LIV-GOLD (548-4653)

PRINCIPAL DISPLAY PANEL - 150 mL Can Label

Australian G old®

HELLO

KITTY

Wet/Dry Skin Formula

Body Mist Sunscreen

Paradise Pineapple

50

BROAD SPECTRUM SPF 50

Water Resistant (80 minutes)

5 FL OZ (150mL)